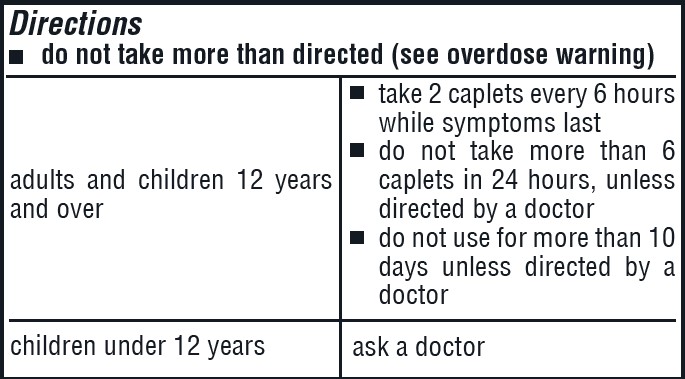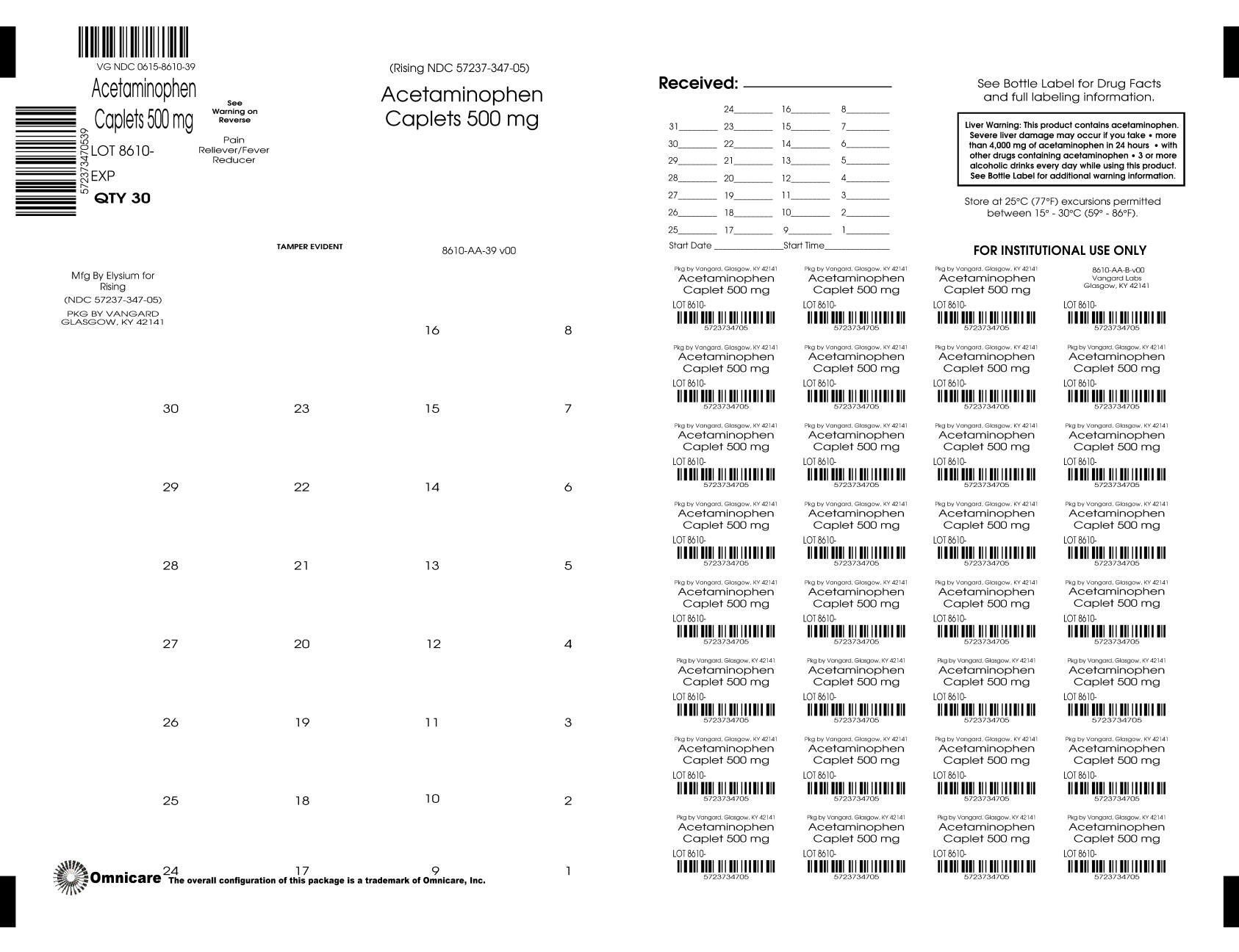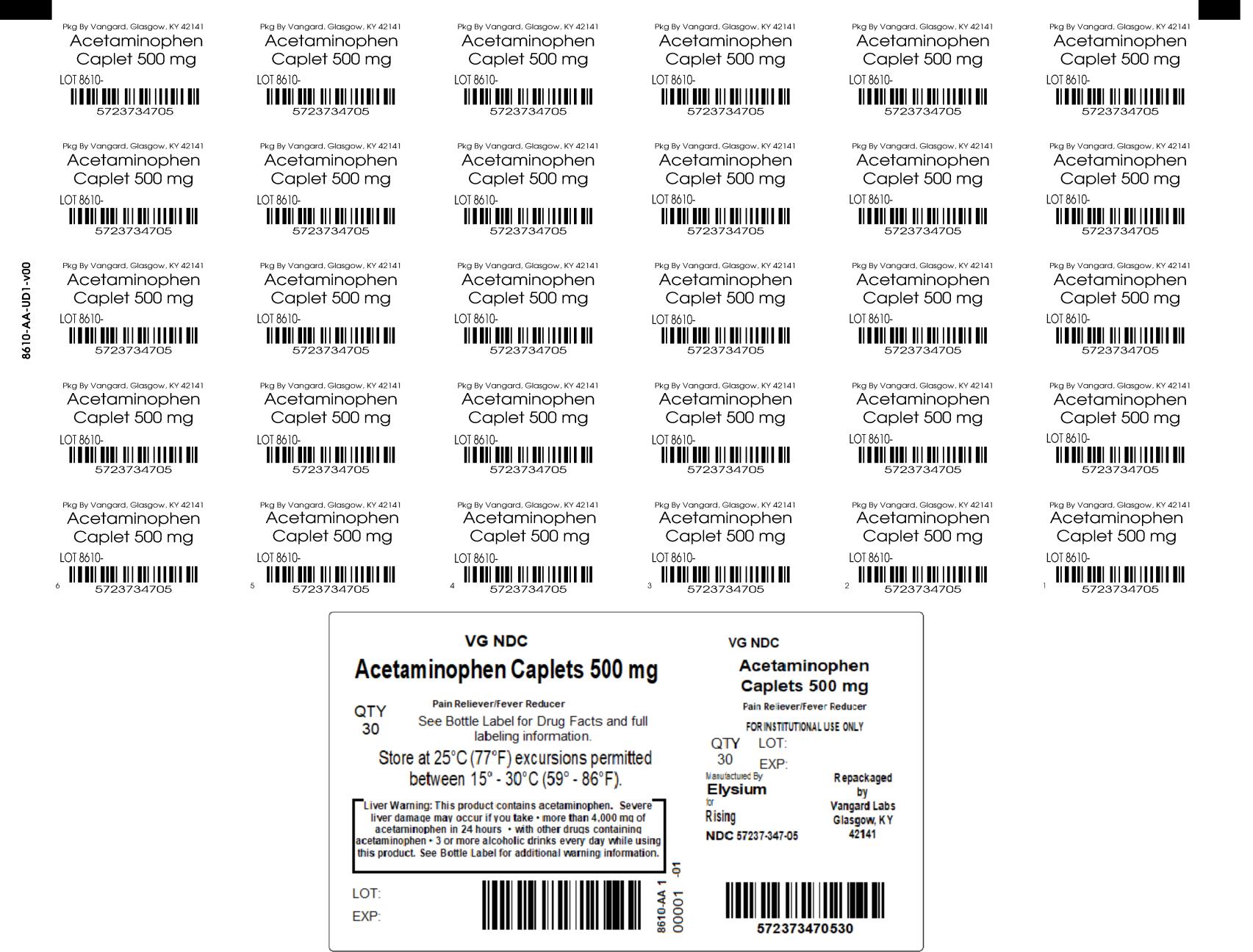 DRUG LABEL: Acetaminophen
NDC: 0615-8610 | Form: TABLET, FILM COATED
Manufacturer: NCS HealthCare of KY, LLC dba Vangard Labs
Category: otc | Type: HUMAN OTC DRUG LABEL
Date: 20260226

ACTIVE INGREDIENTS: ACETAMINOPHEN 500 mg/1 1
INACTIVE INGREDIENTS: HYPROMELLOSE, UNSPECIFIED; MAGNESIUM STEARATE; MICROCRYSTALLINE CELLULOSE; POLYETHYLENE GLYCOL, UNSPECIFIED; POVIDONE; STARCH, CORN; STEARIC ACID; TALC; TITANIUM DIOXIDE

Compare to active ingredient in Tylenol® Extra Strength†
Extra Strength
Acetaminophen
500 mg
* Pain Reliever
* Fever Reducer
* Contains No Aspirin

DO NOT USE IF IMPRINTED SAFETY SEAL UNDER CAP IS BROKEN OR MISSING. Drug Facts

Active Ingredient (in each caplet) Purpose

Acetaminophen USP, 500 mg........................................Pain Reliever/Fever Reducer

Uses

- temporarily relieves minor aches and pains due to:
- the common cold
- headache
- backache
- minor pain from arthritis
- toothache
- muscular aches
- premenstrual and menstrual cramps
- temporarily reduces fever

Warnings

Liver warning: This product contains acetaminophen.

Severe liver damage may occur if you take

- more than 4,000 mg of acetaminophen in 24 hours
- with other drugs containing acetaminophen
- 3 or more alcoholic drinks every day while using this product

Allergy alert: acetaminophen may cause severe skin reactions.

Symptoms may include:

- skin reddening
- blisters
- rash

If a skin reaction occurs, stop use and seek medical help right away.

Do not use

- with any other drug containing acetaminophen (prescription or nonprescription). If you are not sure whether a drug contains acetaminophen, ask a doctor or pharmacist.
- if you are allergic to acetaminophen or any of the inactive ingredients in this product

Ask a doctor before use if you have liver disease

Ask a doctor or pharmacist before use if you are taking the blood thinning drug warfarin

Stop use and ask a doctor if

- pain gets worse or lasts more than 10 days
- fever gets worse or lasts more than 3 days
- new symptoms occur
- redness or swelling is present

These could be signs of a serious condition.

PREGNANCY OR BREAST FEEDING

If pregnant or breast-feeding, ask a health professional before use.

Keep out of reach of children.

Overdose warning: In case of overdose, get medical help or contact a Poison Control Center right away (1-800-222-1222). Prompt medical
attention is critical for adults as well as for children even if you do not notice any signs or symptoms.

Other information

- SODIUM FREE
- store at 25°C (77°F) excursions permitted between 15°-30°C (59°-86°F)
- see end panel for lot number and expiration date.

Inactive ingredients

Hypromellose, magnesium stearate, microcrystalline cellulose, polyethylene glycol, povidone, pregelatinized starch, stearic acid, talc, titanium dioxide

Questions or comments? Call 1-844-474-7464

†This product is neither manufactured nor distributed by the owner of the registered trademark Tylenol® Extra Strength.

Distributed by:
Rising Pharma Holdings, Inc.

East Brunswick, NJ 08816

Made in India

Mfg. Lic. No.: G/25/2258

Revised: 10/2025